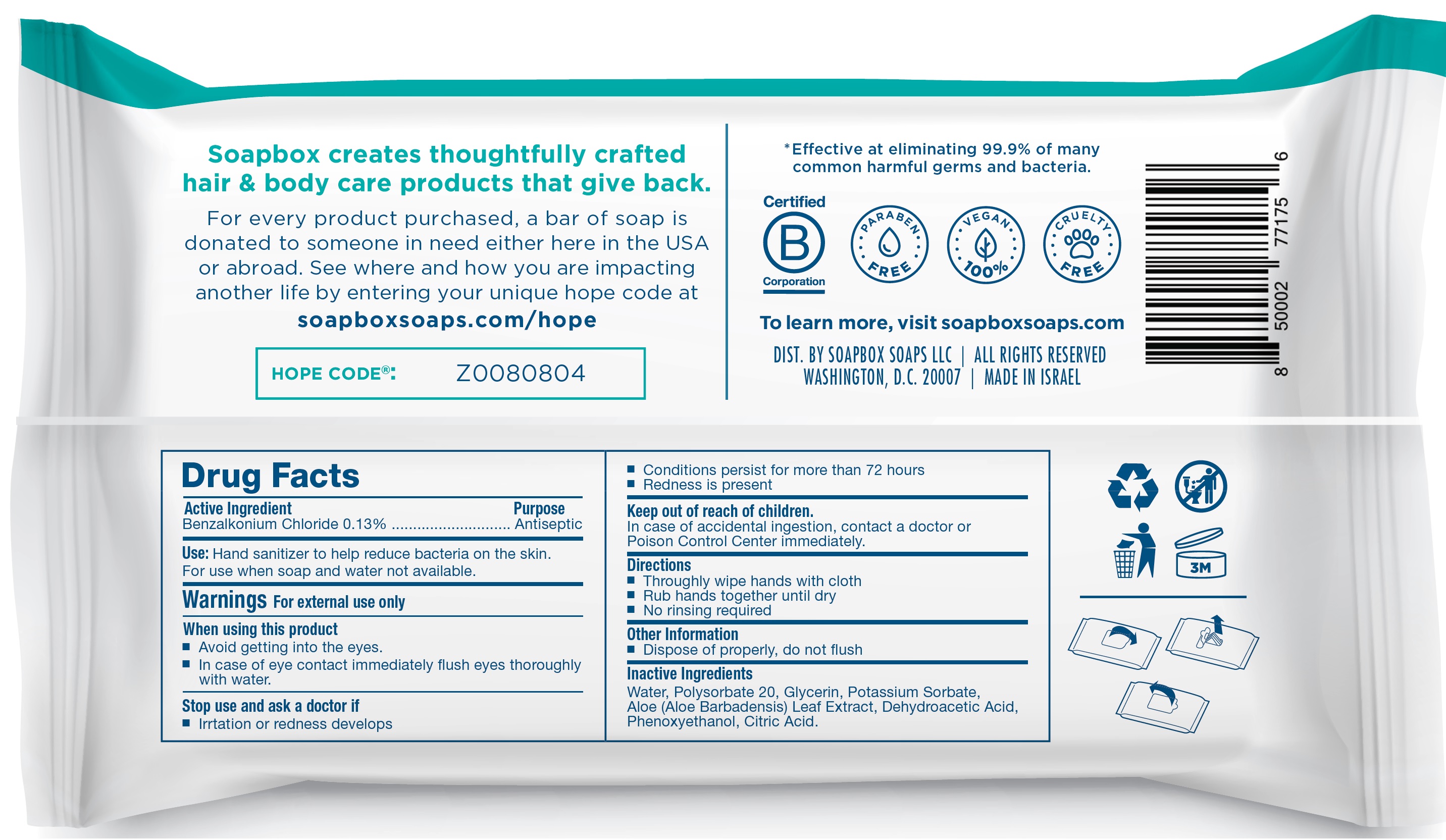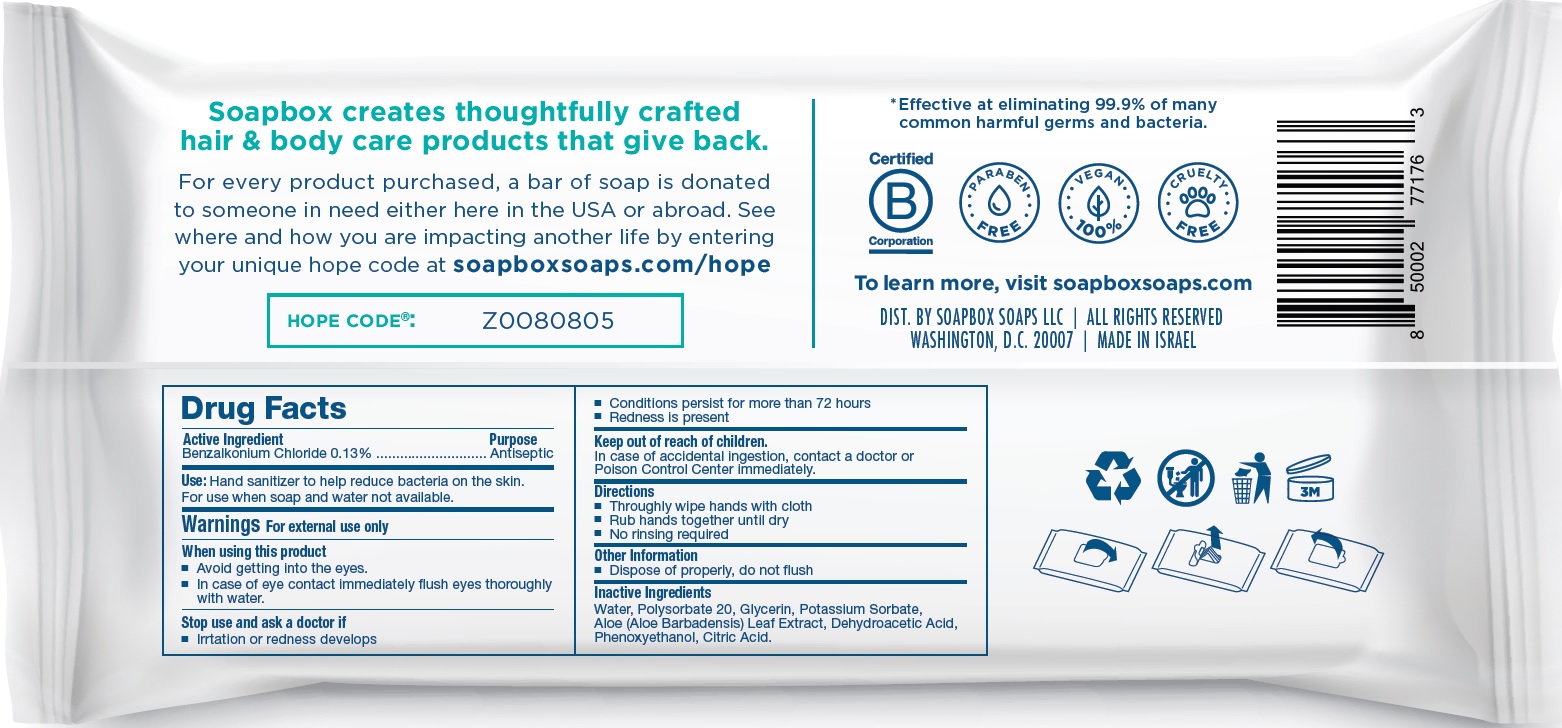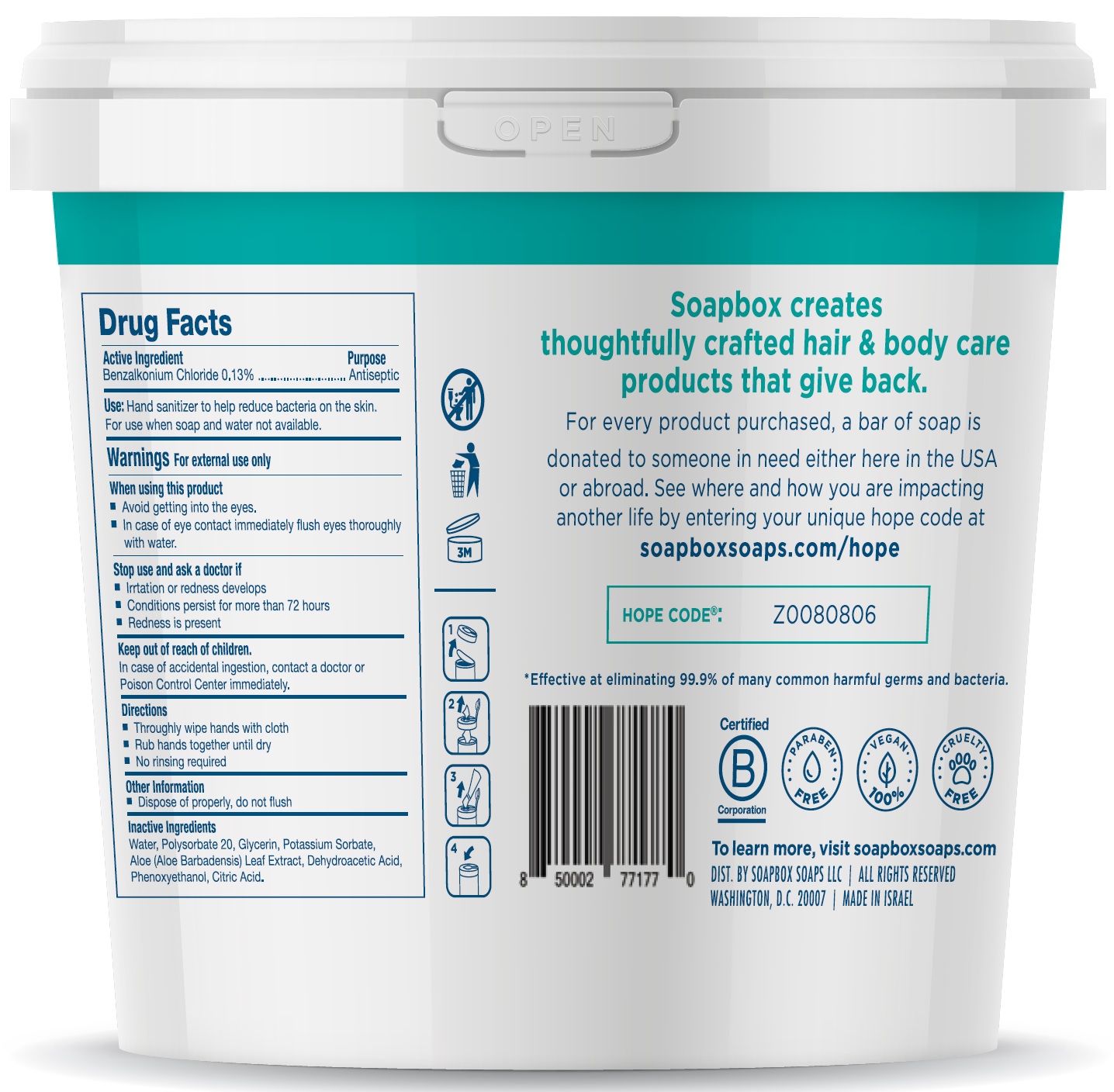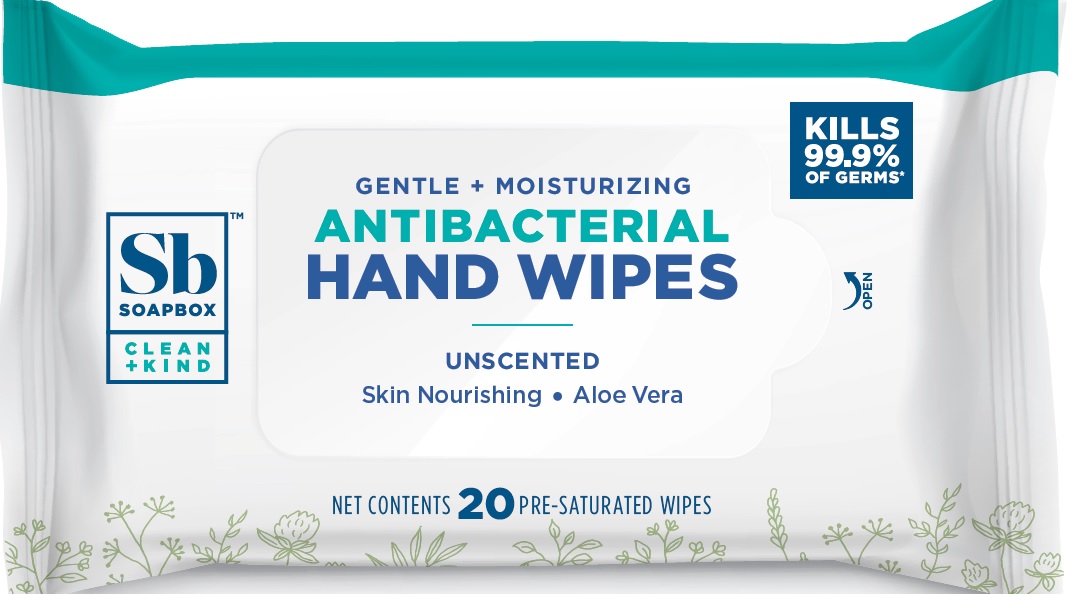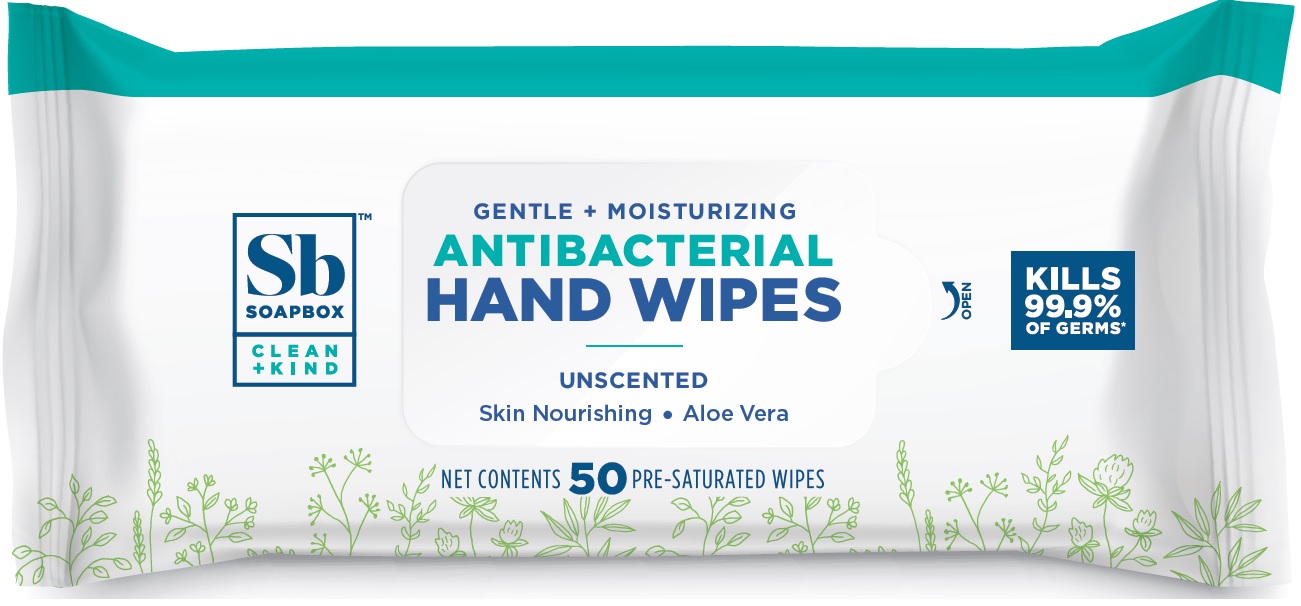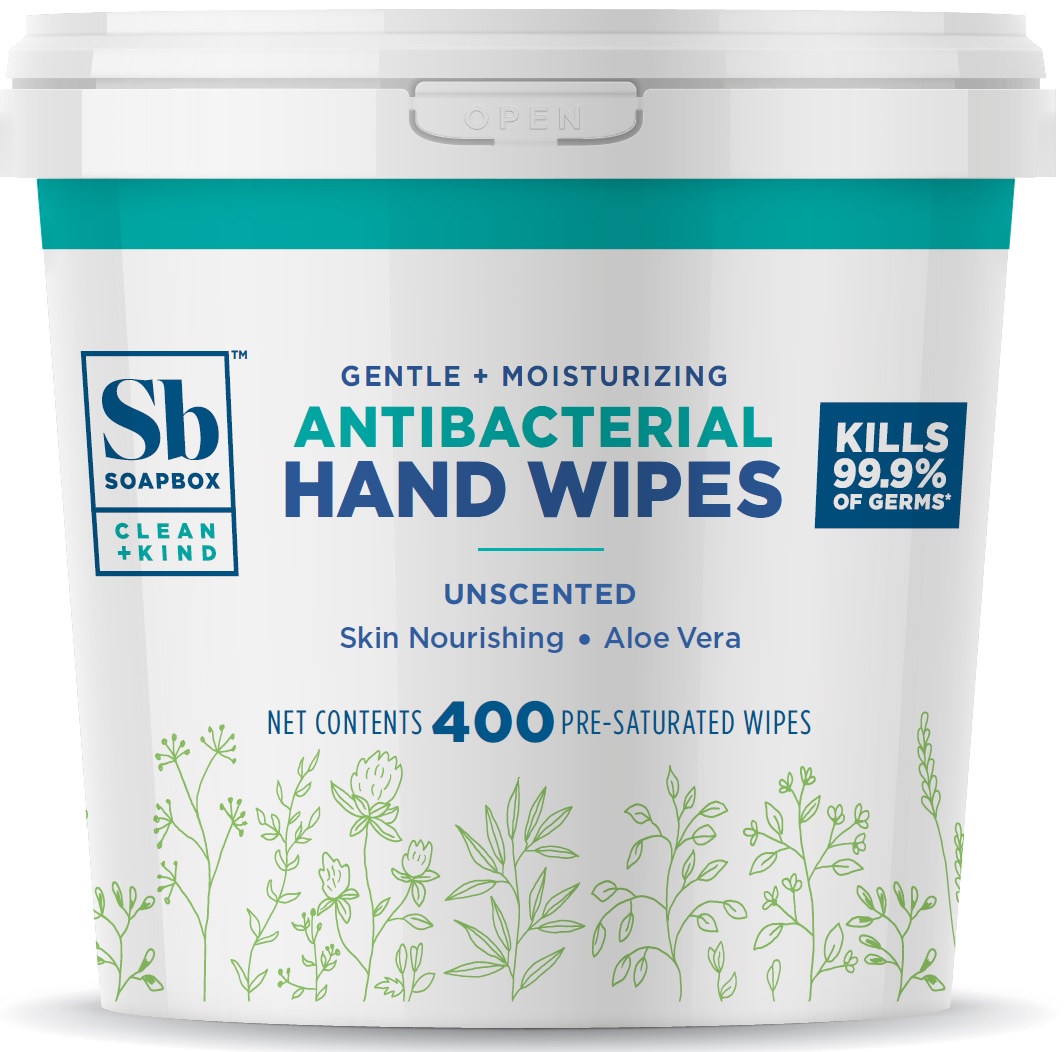 DRUG LABEL: Soapbox Antibacterial Hand Wipes Unscented
NDC: 75115-001 | Form: CLOTH
Manufacturer: Soapbox Soaps, LLC
Category: otc | Type: HUMAN OTC DRUG LABEL
Date: 20201222

ACTIVE INGREDIENTS: BENZALKONIUM CHLORIDE 1.3 mg/1 mL
INACTIVE INGREDIENTS: WATER; POLYSORBATE 20; GLYCERIN; POTASSIUM SORBATE; ALOE VERA LEAF; DEHYDROACETIC ACID; PHENOXYETHANOL; CITRIC ACID MONOHYDRATE

Soapbox Antibacterial Hand Wipes Unscented

Active Ingredient

Benzalkonium Chloride 0.13%

Purpose

Antiseptic

Use:

Hand sanitizer to help reduce bacteria on the skin. For use when soap and water not available.

Warnings

For external use only

When using this product

- Avoid getting into the eyes.
- In case of eye contact immediately flflush eyes thoroughly with water.

Stop use and ask a doctor if

- Irrtation or redness develops
- Conditions persist for more than 72 hours
- Redness is present

Keep out of reach of children.

In case of accidental ingestion, contact a doctor or Poison Control Center immediately.

Directions

- Throughly wipe hands with cloth
- Rub hands together until dry
- No rinsing required

Other Information

- Dispose of properly, do not flush

Inactive Ingredients

Water, Polysorbate 20, Glycerin, Potassium Sorbate, Aloe (Aloe Barbadensis) Leaf Extract, Dehydroacetic Acid, Phenoxyethanol, Citric Acid.